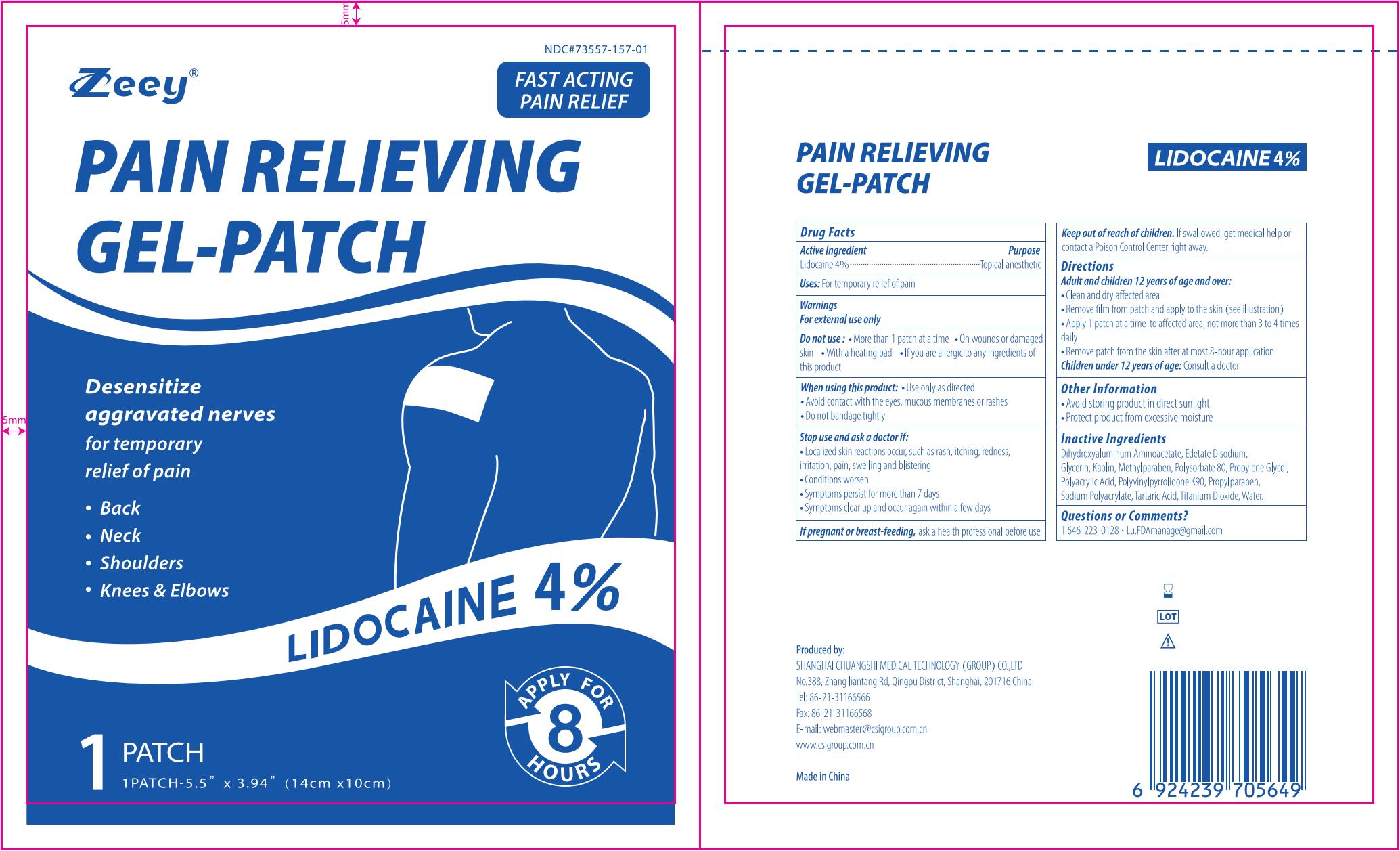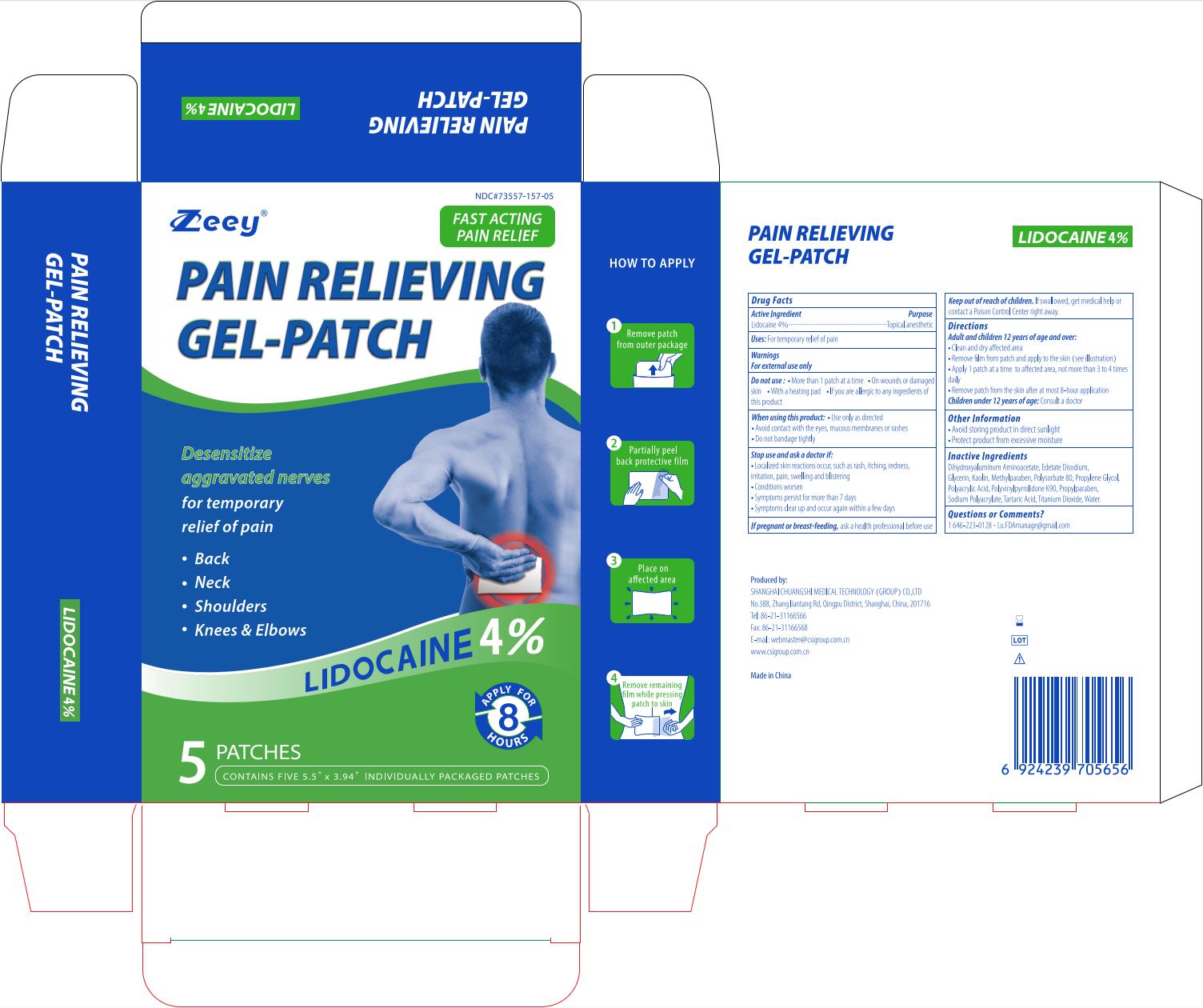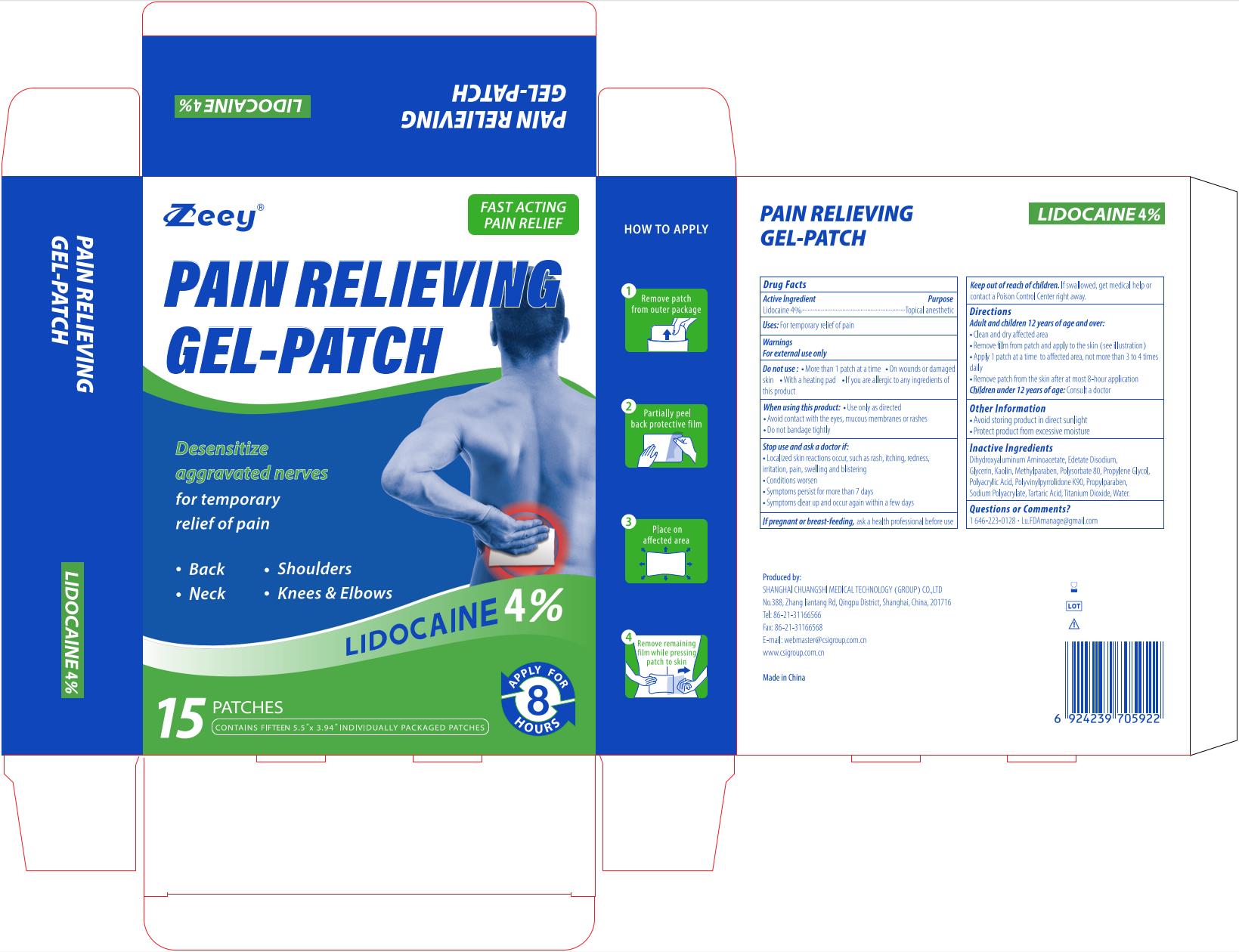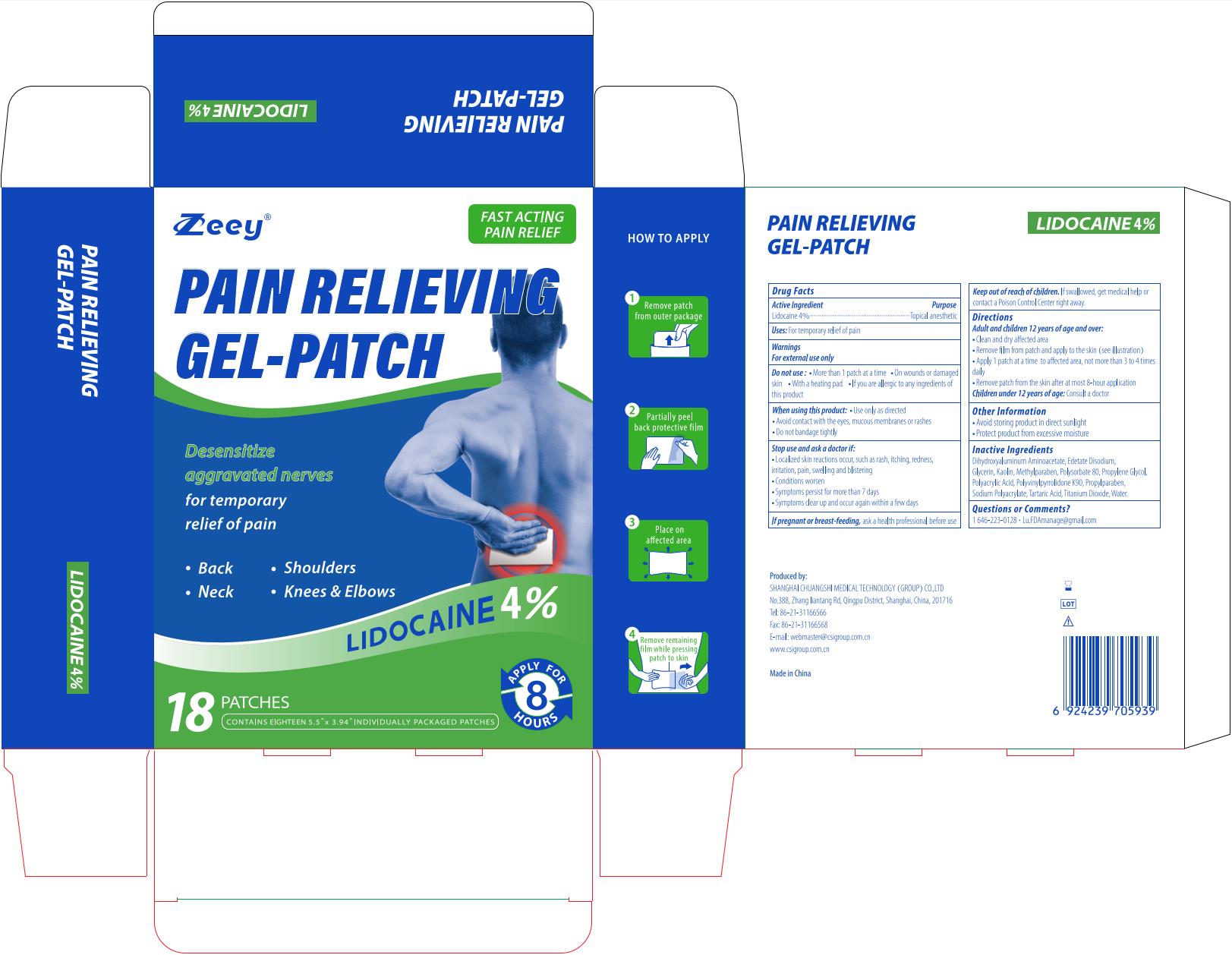 DRUG LABEL: Pain Relieving Gel-Patch
NDC: 73557-157 | Form: PATCH
Manufacturer: Shanghai Chuangshi Medical Technology (Group) Co., Ltd.
Category: otc | Type: HUMAN OTC DRUG LABEL
Date: 20240429

ACTIVE INGREDIENTS: LIDOCAINE 0.04 g/1 g
INACTIVE INGREDIENTS: POLYSORBATE 80; GLYCERIN; POVIDONE K90; METHYLPARABEN; PROPYLPARABEN; EDETATE DISODIUM; KAOLIN; TARTARIC ACID; WATER; PROPYLENE GLYCOL; POLYACRYLIC ACID (250000 MW); SODIUM POLYACRYLATE (2500000 MW); TITANIUM DIOXIDE; DIHYDROXYALUMINUM AMINOACETATE ANHYDROUS

Zeey, Pain Relieving Gel-Patch, Lidocaine 4%, N 5, N 15, N 18

Active ingredient

Lidocaine 4% ...... Purpose: Topical Anesthetic

Purpose

Topical Anesthetic

Uses

For temporary relief of pain

Warnings

For external use only

Ask a doctor if:

- localized skin reactions occur, such as rash, itching, redness, irritation, pain, swelling and blistering
- Conditions worsen
- Symptoms persists for more than 7 days
- Symptoms clear up and occur again within a few days

When using this product

- Use only as directed
- Avoid contact with the eyes, mucous membranes or rashed
- Do not bandage tightly

Do not use

- More than 1 patch at a time
- On wounds or damaged skin
- With a heating pad
- If you are allergic to any ingredients of this product

Stop use if:

- localized skin reactions occur, such as rash, itching, redness, irritation, pain, swelling and blistering
- Conditions worsen
- Symptoms persists for more than 7 days
- Symptoms clear up and occur again within a few days

Pregnancy or breast feeding

If pregnant or breastfeeding, ask a health professional before use

Keep out of reach of children. If swallowed, get medical help or contact a Poison Control Center right away.

Directions

Adult and Children 12 years of age and over:

- Clean and dry affected area
- Remove film from patch and apply to the skin (see illustration)
- Apply 1 patch at a time to affected area, not more than 3 to 4 times daily
- Remove patch from the skin after at most 8-hour application

Children under 12 years of age: Consult a doctor

Dosage forms & strengths

This is a strip, patch dosage form.

The active ingredient strength is 4% w/w.

One patch one time, no more than 8 hours one time.

Inactive ingredients

Glycerin, Sodium Polyacrylate, Dihydroxyaluminum Aminoacetate, Disodium Ethylenediaminetetraacetic Acid, Kaolin, Titanium Dioxide, Polysorbate 80, Propylene Glycol, Tartaric Acid, Polyacrylic Acid, Polyvinylpyrrolidone K90, Methylparaben, Propylparaben, Water

Questions or Comments?

1 646-223-0128 · Lu.FDAmanage@gmail.com

Other information

- Avoid storing product in direct sunlight
- Protect product from excessive moisture